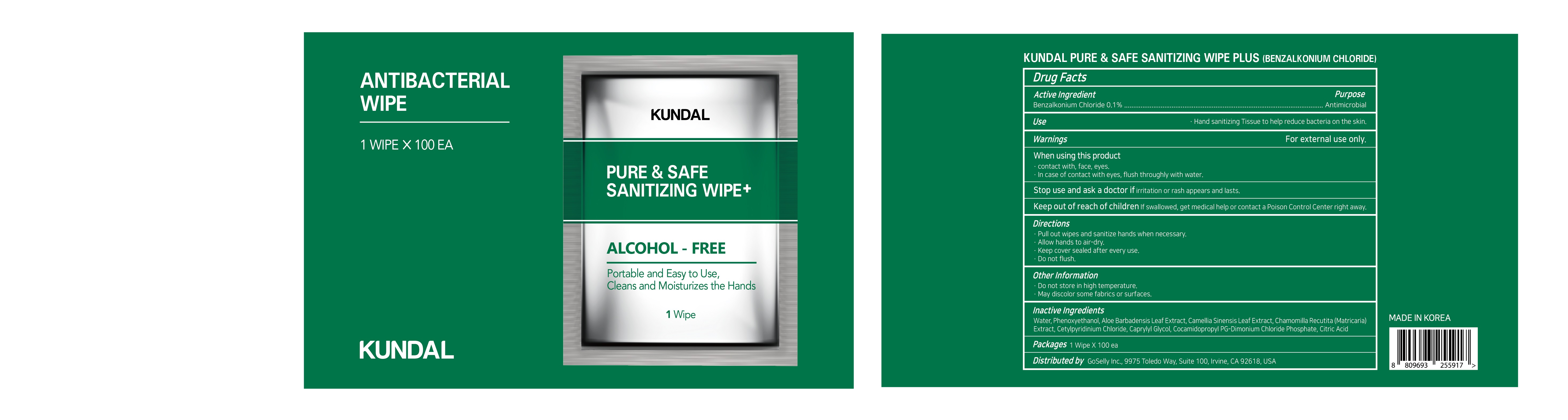 DRUG LABEL: KUNDAL PURE and SAFE SANITIZING TISSUE (BENZALKONIUM CHLORIDE)
NDC: 74773-0027 | Form: LIQUID
Manufacturer: THESKINFACTORY Co., Ltd.
Category: otc | Type: HUMAN OTC DRUG LABEL
Date: 20201116

ACTIVE INGREDIENTS: BENZALKONIUM CHLORIDE 0.1 g/100 g
INACTIVE INGREDIENTS: SODIUM BENZOATE; ALOE VERA LEAF; GREEN TEA LEAF; WATER; CITRIC ACID MONOHYDRATE; MATRICARIA RECUTITA; SODIUM CITRATE; POLYSORBATE 20

ACTIVE INGREDIENT

benzalkonium chloride

INACTIVE INGREDIENT

Water
Aloe Barbadensis Leaf Extract
Camellia Sinensis Leaf Extract
Chamomilla Recutita (Matricaria) Extract
Phenoxyethanol
Cetylpyridinium Chloride
Caprylyl Glycol
Cocamidopropyl PG-Dimonium Chloride Phosphate
Citric Acid

PURPOSE

hand sanitizing tissue to help reduce bacteria on the skin

keep out of reach of the children

INDICATIONS AND USAGE

pull ouy wipes and sanitize hands when necessary

WARNINGS

For external use only. Flammable. Keep away from heat or flame.

Do not use

- in children less than 2 months of age
- on open skin wounds

When using this product keep out of eyes, ears, and mouth. In case of contact with eyes, rinse thoroughly with water.

Stop use and ask a doctor if irritation or rash occurs. These may be signs of a serious condition.

Keep out of reach of children. If swallowed, get medical help or contact a Poison Control Center right away.

DOSAGE AND ADMINISTRATION

for external use only